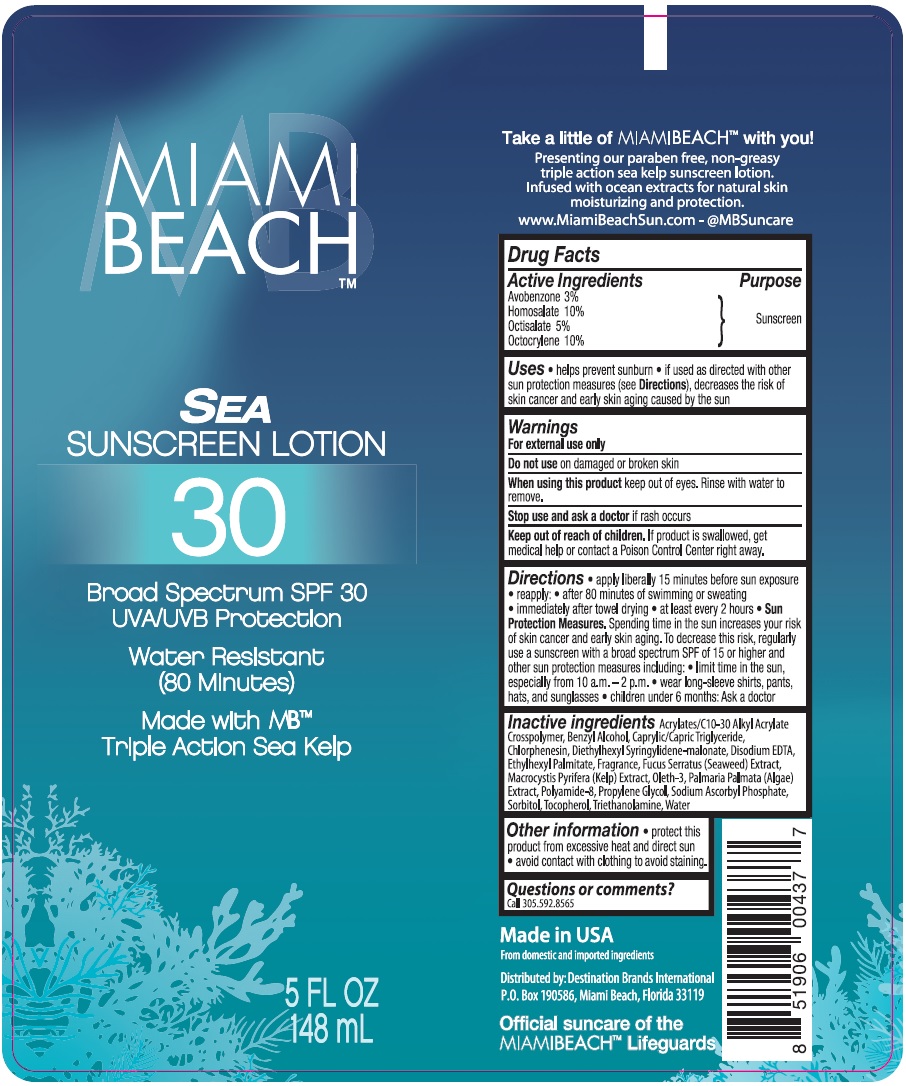 DRUG LABEL: Miami Beach
NDC: 58443-0260 | Form: LOTION
Manufacturer: Prime Enterprises Inc.
Category: otc | Type: HUMAN OTC DRUG LABEL
Date: 20200117

ACTIVE INGREDIENTS: OCTOCRYLENE 99.6 mg/1 mL; AVOBENZONE 29.88 mg/1 mL; OCTISALATE 49.8 mg/1 mL; HOMOSALATE 99.6 mg/1 mL
INACTIVE INGREDIENTS: TROLAMINE; ETHYLHEXYL PALMITATE; OLETH-3; DULSE; PROPYLENE GLYCOL; SORBITOL; EDETATE DISODIUM; CARBOMER 1342; BENZYL ALCOHOL; MEDIUM-CHAIN TRIGLYCERIDES; FUCUS SERRATUS; POLYAMIDE-8 (4500 MW); CHLORPHENESIN; DIETHYLHEXYL SYRINGYLIDENEMALONATE; MACROCYSTIS PYRIFERA; SODIUM ASCORBYL PHOSPHATE; TOCOPHEROL; WATER

Miami Beach Sea Sunscreen Lotion 30 Broad Spectrum SPF 30

Active Ingredients

Avobenzone 3%

Homosalate 10%

Octisalate 5%

Octocrylene 10%

Purpose

Sunscreen

Uses

• helps prevent sunburn • if used as directed with other sun protection measures (see Directions), decreases the risk of skin cancer and early skin aging caused by the sun.

Warnings

For external use only

Do not use on damaged or broken skin

When using this product keep out of eyes. Rinse with water to remove.

Stop use and ask a doctor if rash occurs

Keep out of reach of children. If product is swallowed, get medical help or contact a Poison Control Center right away.

Directions

• apply liberally 15 minutes before sun exposure

• reapply: • after 80 minutes of swimming or sweating

• immediately after towel drying • at least every 2 hours • Sun Protection Measures. Spending time in the sun increases your risk of skin cancer and early skin aging. To decrease this risk, regularly use a sunscreen with broad spectrum SPF of 15 or higher and other sun protection measures including: • limit time in the sun, especially from 10 a.m. – 2 p.m. • wear long-sleeve shirts, pants, hats, and sunglasses • children under 6 months: Ask a doctor

Inactive ingredients

Acrylates/C10-30 Alkyl Acrylate Crosspolymer, Benzyl Alcohol, Caprylic/Capric Triglyceride, Chlorphenesin, Diethylhexyl Syringylidene-malonate, Disodium EDTA, Ethylhexyl Palmitate, Fragrance, Fucus Serratus (Seaweed) Extract, Macrocystis Pyrifera (Kelp) Extract, Oleth-3, Palmaria Palmata (Algae) Extract, Polyamide-8, Propylene Glycol, Sodium Ascorbyl Phosphate, Sorbitol, Tocopherol, Triethanolamine, Water

Other information

• protect this product from excessive heat and direct sun. • avoid contact with clothing to avoid staining.

Questions or comments?

Call 305.592.8565